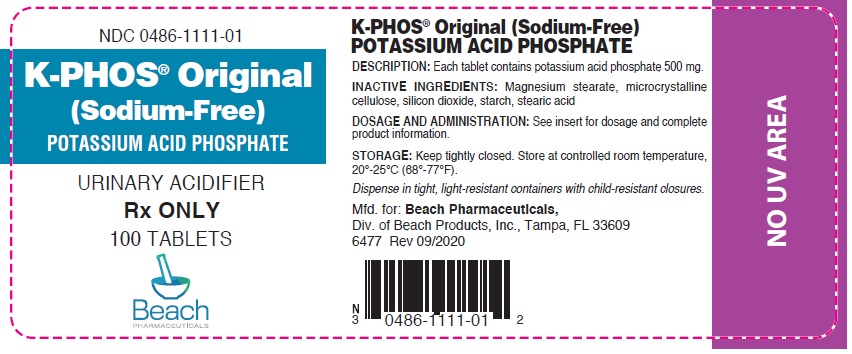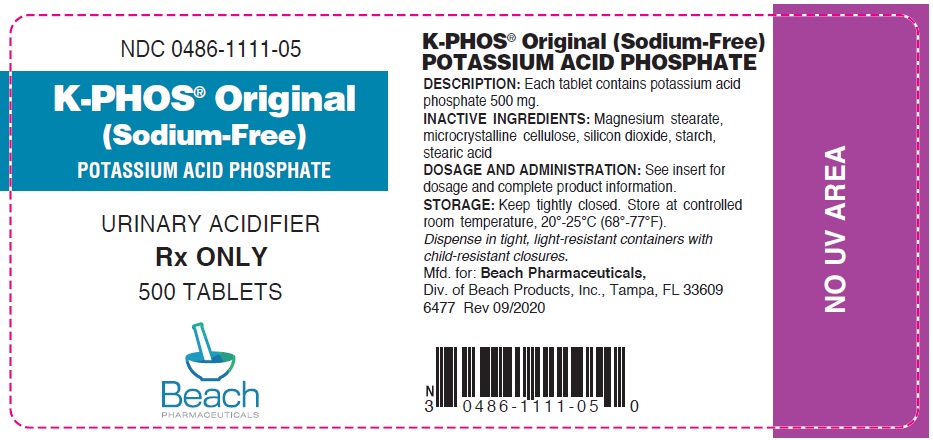 DRUG LABEL: K Phos

NDC: 0486-1111 | Form: TABLET, SOLUBLE
Manufacturer: Beach Products, Inc.
Category: prescription | Type: HUMAN PRESCRIPTION DRUG LABEL
Date: 20230223

ACTIVE INGREDIENTS: POTASSIUM PHOSPHATE, MONOBASIC 500 mg/1 1
INACTIVE INGREDIENTS: CELLULOSE, MICROCRYSTALLINE; SILICON DIOXIDE; STARCH, CORN; STEARIC ACID; MAGNESIUM STEARATE

K-PHOS® ORIGINAL
Potassium Acid Phosphate

Rx ONLY

DESCRIPTION

Each tablet contains potassium acid phosphate 500 mg. Each tablet yields approximately 114 mg of phosphorus and 144 mg of potassium or 3.7 mEq.

Inactive ingredients: Magnesium stearate, microcrystalline cellulose, silicon dioxide, starch, stearic acid.

ACTIONS

K-PHOS® ORIGINAL is a highly effective sodium-free urinary acidifier.

INDICATONS AND USAGE

For use in patients with elevated urinary pH. K-PHOS® ORIGINAL helps keep calcium soluble and reduces odor and rash caused by ammoniacal urine. Also, by acidifying the urine, it increases the antibacterial activity of methenamine mandelate and methenamine hippurate.

CONTRAINDICATIONS

This product is contraindicated in patients with infected phosphate stones; in patients with severely impaired renal function (less than 30% of normal) and in the presence of hyperphosphatemia and hyperkalemia.

PRECAUTIONS

General

This product contains potassium and should be used with caution if regulation of this element is desired. Occasionally, some individuals may experience a mild laxative effect during the first few days of phosphate therapy. If laxation persists to an unpleasant degree, reduce the daily dosage until this effect subsides or, if necessary, discontinue the use of this product.

Caution should be exercised when prescribing this product in the following conditions: Cardiac disease (particularly in digitalized patients); severe adrenal insufficiency (Addison's disease); acute dehydration; severe renal insufficiency or chronic renal disease; extensive tissue breakdown (such as severe burns); myotonia congenita; hypoparathyroidism; and acute pancreatitis. Rickets may benefit from phosphate therapy, but caution should be exercised. High serum phosphate levels may increase the incidence of extra-skeletal calcification.

Information for Patients

Patients with kidney stones may pass old stones when phosphate therapy is started and should be warned of this possibility. Patients should be advised to avoid the use of antacids containing aluminum, calcium, or magnesium, which may prevent the absorption of phosphate. To assure against gastrointestinal injury associated with oral ingestion of concentrated potassium salt preparations, patients should be instructed to dissolve tablets completely in an appropriate amount of water before taking.

Laboratory Tests

Careful monitoring of renal function and serum calcium, phosphorus and potassium may be required at periodic intervals during potassium phosphate therapy. Other tests may be warranted in some patients, depending on conditions.

Drug Interactions

The use of antacids containing magnesium, calcium, or aluminum in conjunction with phosphate preparations may bind the phosphate and prevent its absorption. Potassium-containing medications or potassium-sparing diuretics may cause hyperkalemia when used concurrently with potassium salts. Patients should have serum potassium level determinations at periodic intervals. Concurrent use of salicylates may lead to increased serum salicylate levels since excretion of salicylates is reduced in acidified urine. Serum salicylate levels should be closely monitored to avoid toxicity.

Carcinogenesis, Mutagenesis, Impairment of Fertility

No long-term or reproduction studies in animals or humans have been performed with K-PHOS® ORIGINAL to evaluate its carcinogenic, mutagenic, or impairment of fertility potential.

Pregnancy

Teratogenic Effects

Pregnancy Category C

Animal reproduction studies have not been conducted with K-PHOS® ORIGINAL. It is also not known whether this product can cause fetal harm when administered to a pregnant woman or can affect reproductive capacity. This product should be given to a pregnant woman only if clearly needed.

Nursing Mothers

It is not known whether this drug is excreted in human milk. Because many drugs are excreted in human milk, caution should be exercised when this product is administered to a nursing woman.

ADVERSE REACTIONS

Gastrointestinal upset (diarrhea, nausea, stomach pain, and vomiting) may occur with the use of potassium phosphate. Also, bone and joint pain (possible phosphate-induced osteomalacia) could occur. The following adverse effects may be observed with potassium administration: irregular heartbeat; dizziness; mental confusion; weakness or heaviness of legs; unusual tiredness; muscle cramps; numbness, tingling, pain, or weakness in hands or feet; numbness or tingling around lips; shortness of breath or troubled breathing.

DOSAGE AND ADMINISTRATION

Two tablets dissolved in 6-8 oz. of water 4 times daily with meals and at bedtime. For best results, let the tablets soak in water for 2 to 5 minutes, or more if necessary, and stir. If any tablet particles remain undissolved, they may be crushed and stirred vigorously to speed dissolution.

HOW SUPPLIED

White, scored tablet with the name BEACH and the number 1111 imprinted on each tablet. Bottles of 100 (NDC 0486-1111-01) and bottles of 500 (NDC 0486-1111-05) tablets.

STORAGE

Keep tightly closed. Store at controlled room temperature, 20°-25°C (68°-77°F).

Dispense in tight, light-resistant containers with child-resistant closures.

BEACH PHARMACEUTICALS, Div. of Beach Products, Inc., Tampa, FL 33609

6477 Rev 09/2020

PRINCIPAL DISPLAY PANEL - 100 Tablet Bottle Label

NDC 0486-1111-01

K-PHOS® Original
(Sodium-Free)
POTASSIUM ACID PHOSPHATE

URINARY ACIDIFIER

Rx ONLY

100 TABLETS

Beach
PHARMACEUTICALS

PRINCIPAL DISPLAY PANEL - 500 Tablet Bottle Label

NDC 0486-1111-05

K-PHOS® Original
(Sodium-Free)
POTASSIUM ACID PHOSPHATE

URINARY ACIDIFIER

Rx ONLY

500 TABLETS

Beach
PHARMACEUTICALS